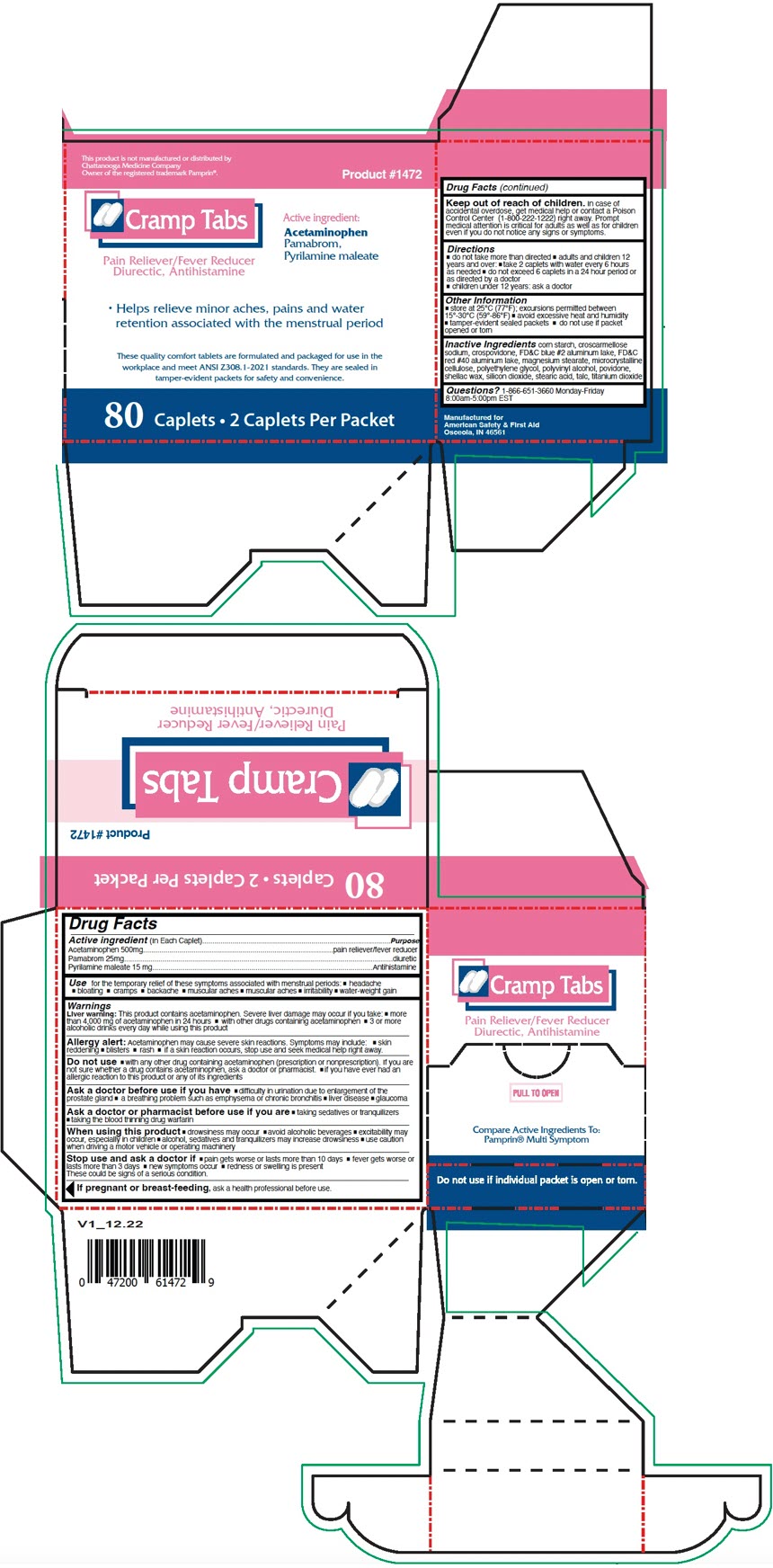 DRUG LABEL: Cramp Tabs
NDC: 73598-1472 | Form: CAPSULE, COATED
Manufacturer: JHK DBA American Safety & First Aid
Category: otc | Type: HUMAN OTC DRUG LABEL
Date: 20241004

ACTIVE INGREDIENTS: ACETAMINOPHEN 500 mg/1 1; PAMABROM 25 mg/1 1; PYRILAMINE MALEATE 15 mg/1 1
INACTIVE INGREDIENTS: STARCH, CORN; CROSCARMELLOSE SODIUM; CROSPOVIDONE, UNSPECIFIED; FD&C BLUE NO. 1 ALUMINUM LAKE; FD&C RED NO. 40 ALUMINUM LAKE; MAGNESIUM STEARATE; MICROCRYSTALLINE CELLULOSE; POLYETHYLENE GLYCOL, UNSPECIFIED; POLYVINYL ALCOHOL, UNSPECIFIED; POVIDONE, UNSPECIFIED; SHELLAC; SILICON DIOXIDE; STEARIC ACID; TALC; TITANIUM DIOXIDE

Cramp Tabs

Drug Facts

ACTIVE INGREDIENT

Active ingredient (In Each Caplet) | Purpose
Acetaminophen 500mg | pain reliever/fever reducer
Pamabrom 25mg | diuretic
Pyrilamine maleate 15 mg | Antihistamine

Use

for the temporary relief of these symptoms associated with menstrual periods:

- headache
- bloating
- cramps
- backache
- muscular aches
- muscular aches
- irritability
- water-weight gain

Warnings

Liver warning

This product contains acetaminophen. Severe liver damage may occur if you take:

- more than 4,000 mg of acetaminophen in 24 hours
- with other drugs containing acetaminophen
- 3 or more alcoholic drinks every day while using this product

Allergy alert

Acetaminophen may cause severe skin reactions. Symptoms may include:

- skin reddening
- blisters
- rash
- if a skin reaction occurs, stop use and seek medical help right away.

Do not use

- with any other drug containing acetaminophen (prescription or nonprescription). If you are not sure whether a drug contains acetaminophen, ask a doctor or pharmacist.
- if you have ever had an allergic reaction to this product or any of its ingredients

Ask a doctor before use if you have

- difficulty in urination due to enlargement of the prostate gland
- a breathing problem such as emphysema or chronic bronchitis
- liver disease
- glaucoma

Ask a doctor or pharmacist before use if you are

- taking sedatives or tranquilizers
- taking the blood thinning drug warfarin

When using this product

- drowsiness may occur
- avoid alcoholic beverages
- excitability may occur, especially in children
- alcohol, sedatives and tranquilizers may increase drowsiness
- use caution when driving a motor vehicle or operating machinery

Stop use and ask a doctor if

- pain gets worse or lasts more than 10 days
- fever gets worse or lasts more than 3 days
- new symptoms occur
- redness or swelling is present These could be signs of a serious condition.

PREGNANCY OR BREAST FEEDING

If pregnant or breast-feeding, ask a health professional before use.

Keep out of reach of children. In case of accidental overdose, get medical help or contact a Poison Control Center (1-800-222-1222) right away. Prompt medical attention is critical for adults as well as for children even if you do not notice any signs or symptoms.

Directions

- do not take more than directed
- adults and children 12 years and over:
  - take 2 caplets with water every 6 hours as needed
  - do not exceed 6 caplets in a 24 hour period or as directed by a doctor
- children under 12 years: ask a doctor

Other Information

- store at 25°C (77°F); excursions permitted between 15°-30°C (59°-86°F)
- avoid excessive heat and humidity
- tamper-evident sealed packets
- do not use if packet opened or torn

Inactive Ingredients

corn starch, croscarmellose sodium, crospovidone, FD&C blue #2 aluminum lake, FD&C red #40 aluminum lake, magnesium stearate, microcrystalline cellulose, polyethylene glycol, polyvinyl alcohol, povidone, shellac wax, silicon dioxide, stearic acid, talc, titanium dioxide

Questions?

1-866-651-3660 Monday-Friday
8:00am-5:00pm EST

PRINCIPAL DISPLAY PANEL - 2 Capsule Packet Box

This product is not manufactured or distributed by
Chattanooga Medicine Company
Owner of the registered trademark Pamprin®.

Product #1472

Cramp Tabs

Pain Reliever/Fever Reducer
Diurectic, Antihistamine

Active ingredient:

Acetaminophen
Pamabrom,
Pyrilamine maleate

- Helps relieve minor aches, pains and water
  retention associated with the menstrual period

These quality comfort tablets are formulated and packaged for use in the
workplace and meet ANSI Z308.1-2021 standards. They are sealed in
tamper-evident packets for safety and convenience.

80 Caplets ∙ 2 Caplets Per Packet